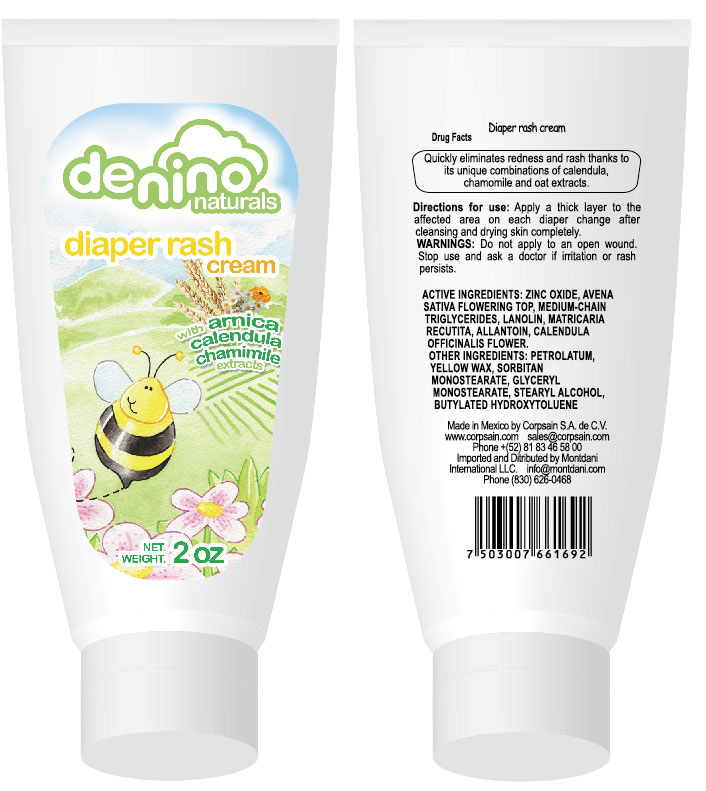 DRUG LABEL: DeNino Diaper Rash
NDC: 50760-8051 | Form: CREAM
Manufacturer: Corpsain SA de CV
Category: otc | Type: HUMAN OTC DRUG LABEL
Date: 20100226

ACTIVE INGREDIENTS: ZINC OXIDE 7.8 mL/60 mL; AVENA SATIVA FLOWERING TOP .6 mL/60 mL; MEDIUM-CHAIN TRIGLYCERIDES 18.21 mL/60 mL; LANOLIN 2.4 mL/60 mL
INACTIVE INGREDIENTS: PETROLATUM; WAX, YELLOW; SORBITAN MONOSTEARATE; GLYCERYL MONOSTEARATE; STEARYL ALCOHOL; PHENOXYETHANOL; BUTYLATED HYDROXYTOLUENE

Diaper Rash Cream. Drug Facts

Drug Facts

Quickly eliminates redness and Rash thanks to its unique combination of calendula, chamomile and oat extracts.

Directions for use: Apply a thick layer to the affected area on each diaper change, after cleansing and drying skin completely.

WARNINGS

Warnings: Do not apply to an open wound. Stop use and ask doctor if irritation or rash persists.

ACTIVE INGREDIENT

Zinc oxide, Avena Sativa Flowering Top, Medium-Chain Triglycerides, Lanolin, Matricaria Recutita, Allantoin, Calendula Officinalis Flower.

INACTIVE INGREDIENT

Other Ingredients: Petrolatum, Yellow Wax, Sorbitan Monostereate, Glycerlyl Monostearate, Stearyl Alcohol, Butylated Hydroxytoluene.

REFERENCES

Made in Mexico by Corpsain SA de CV.

www.corpsain.com sales@corpsain.com

Phone +(52) 81 83 46 5800

Imported and Distributed by Montdani International LCC. info@Montdani.com

Phone (830) 626 0468